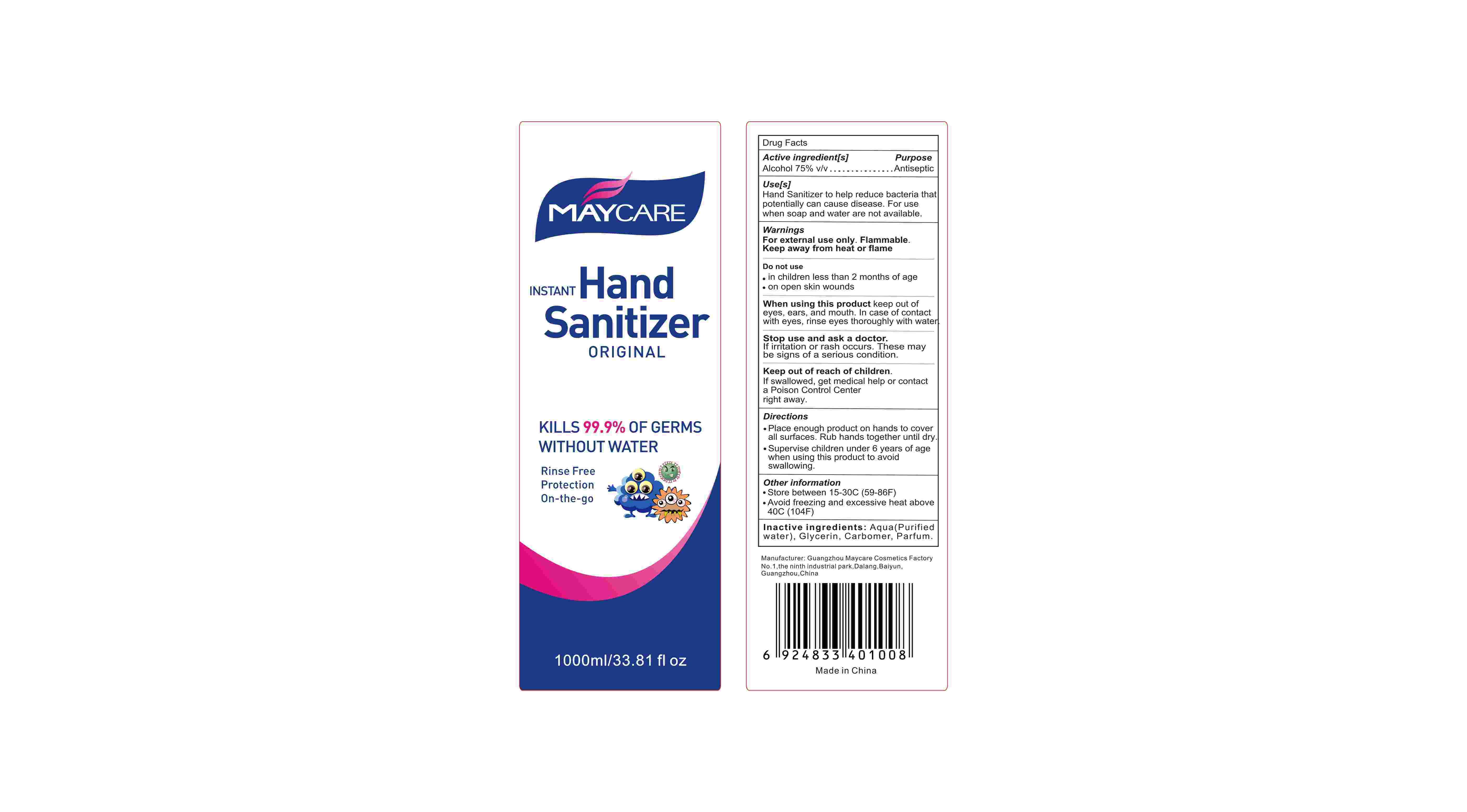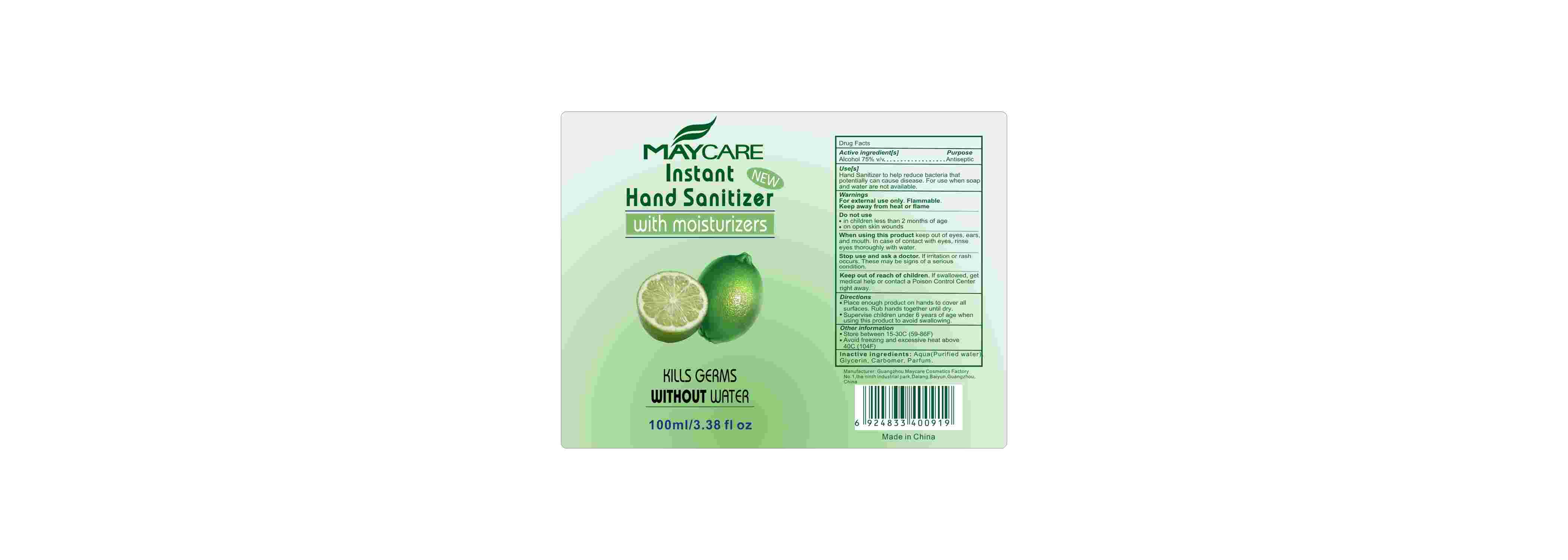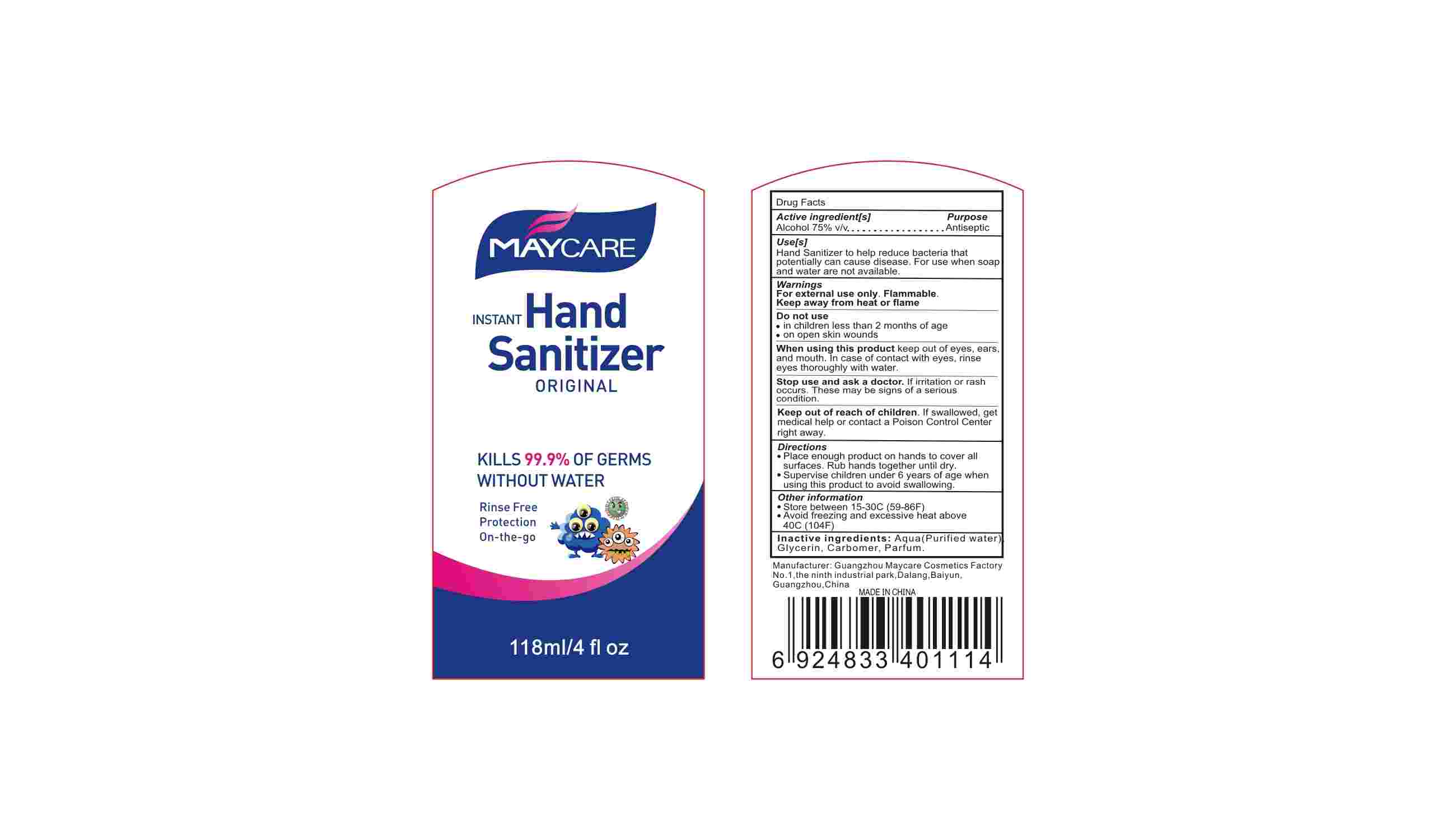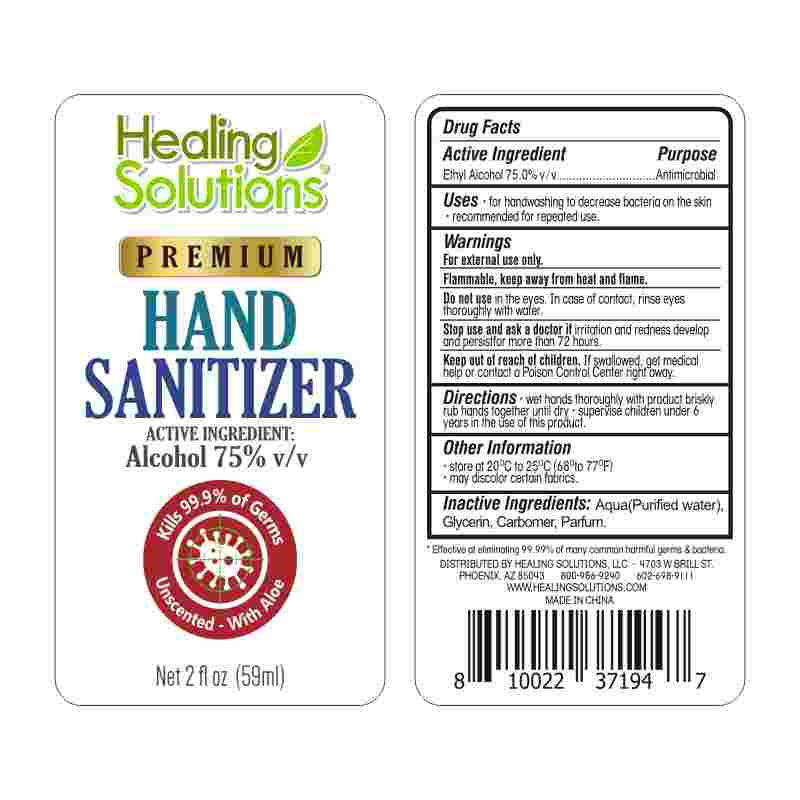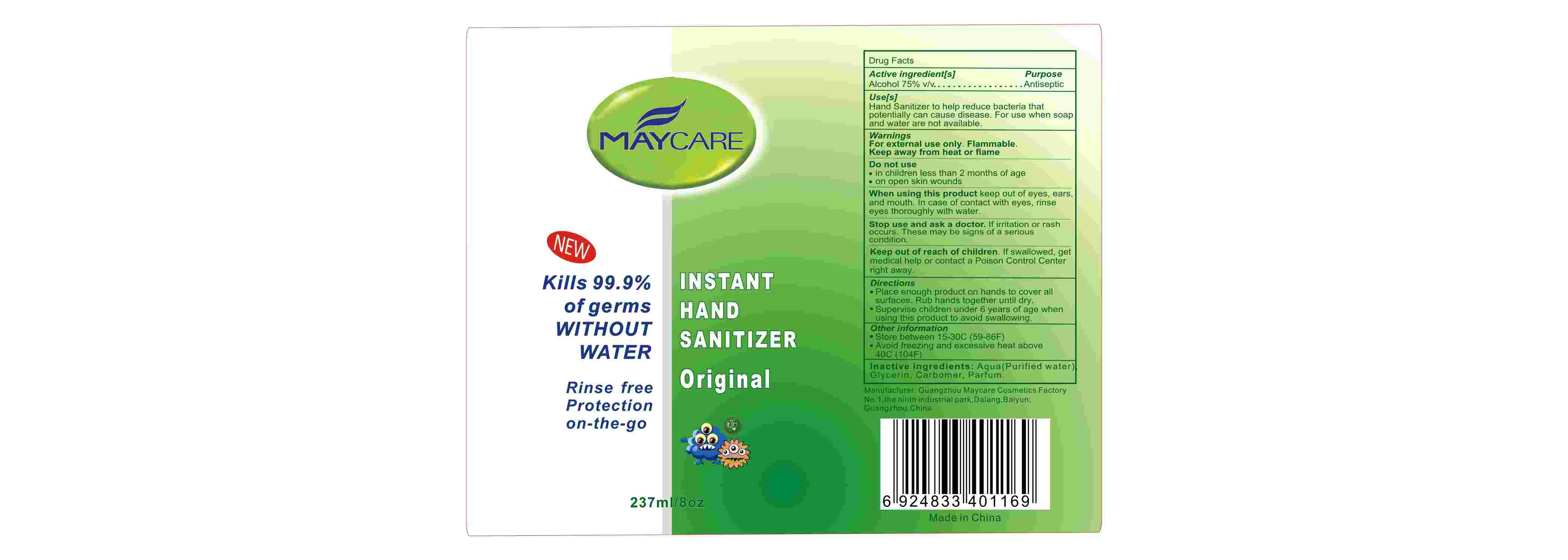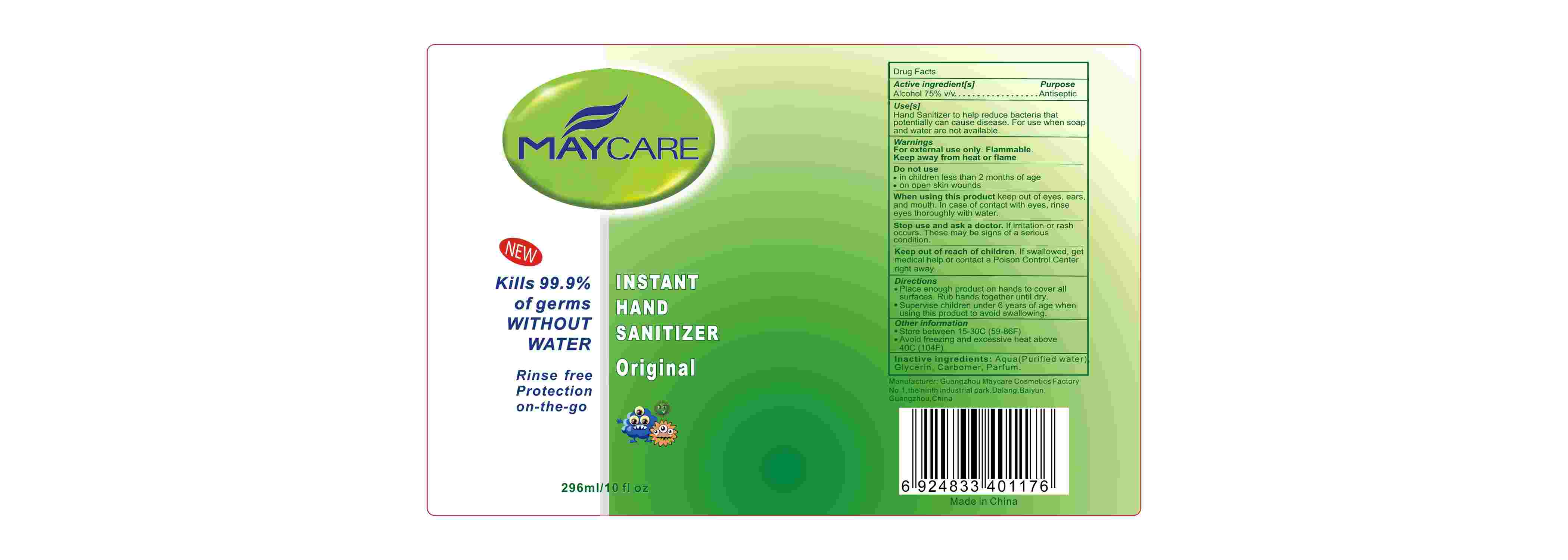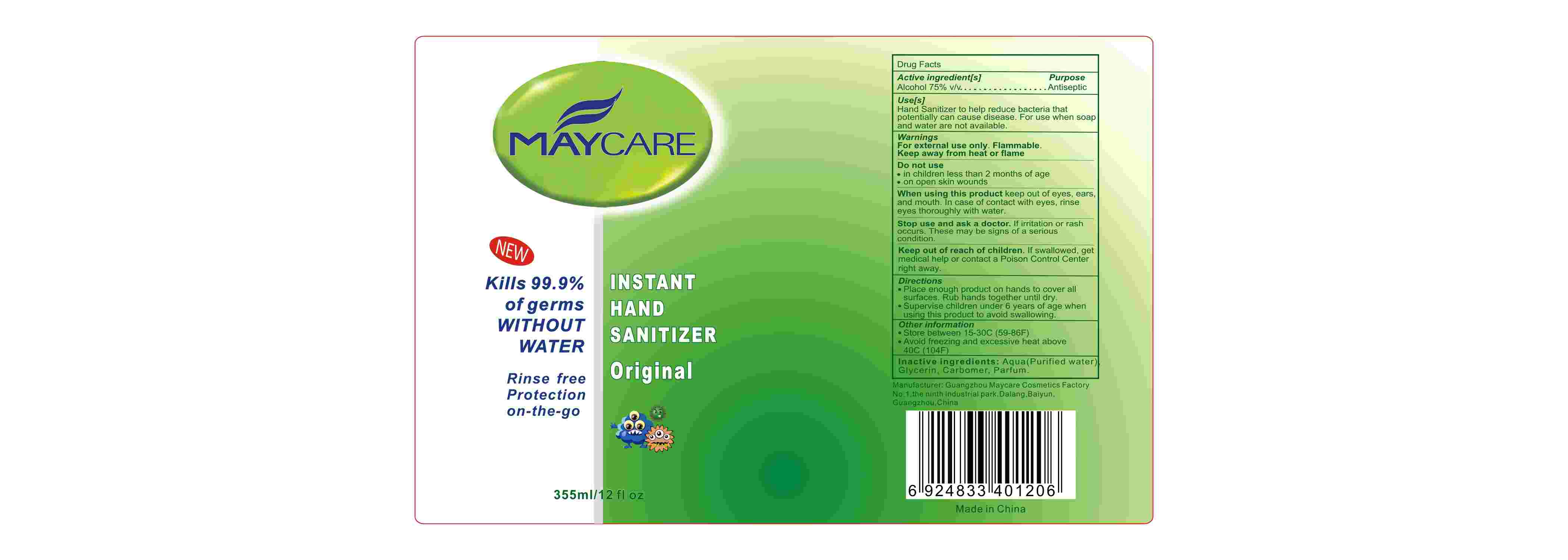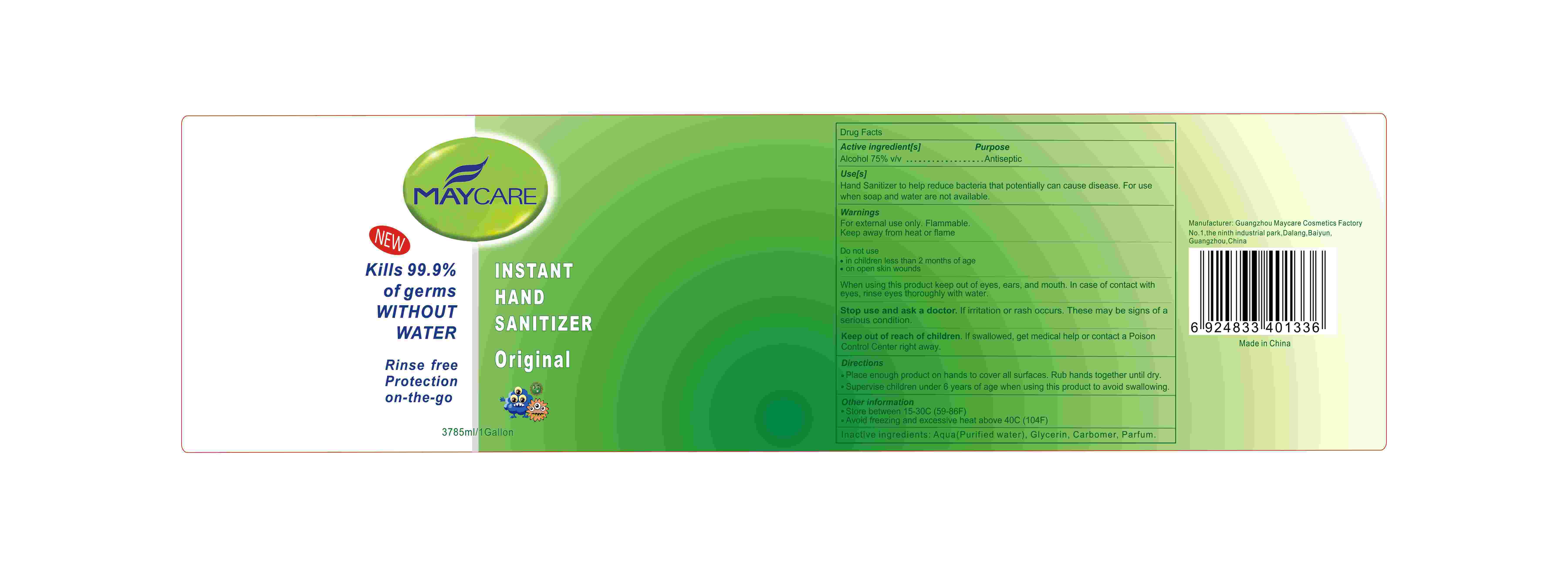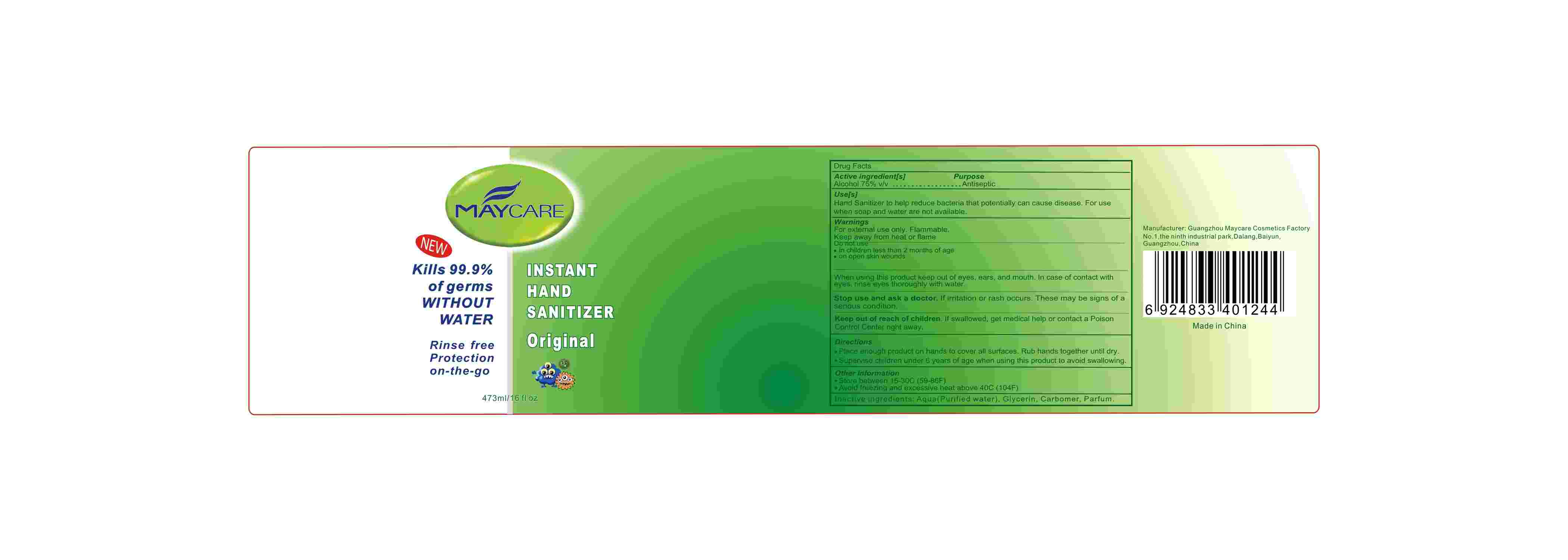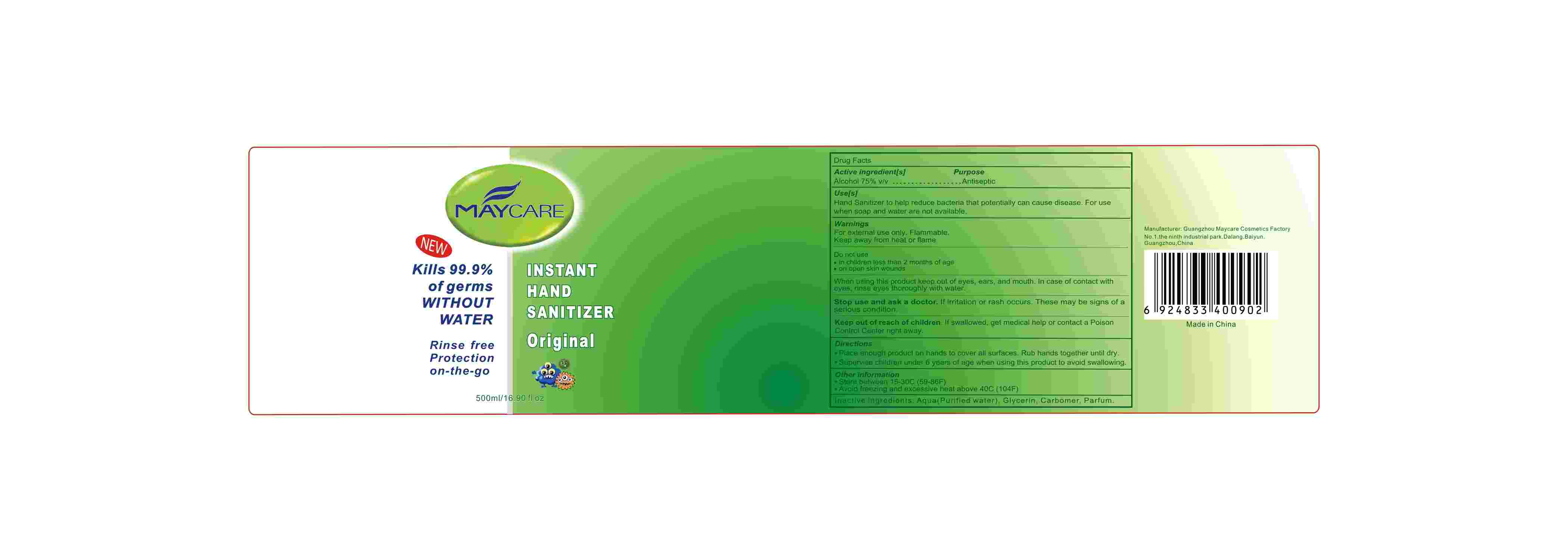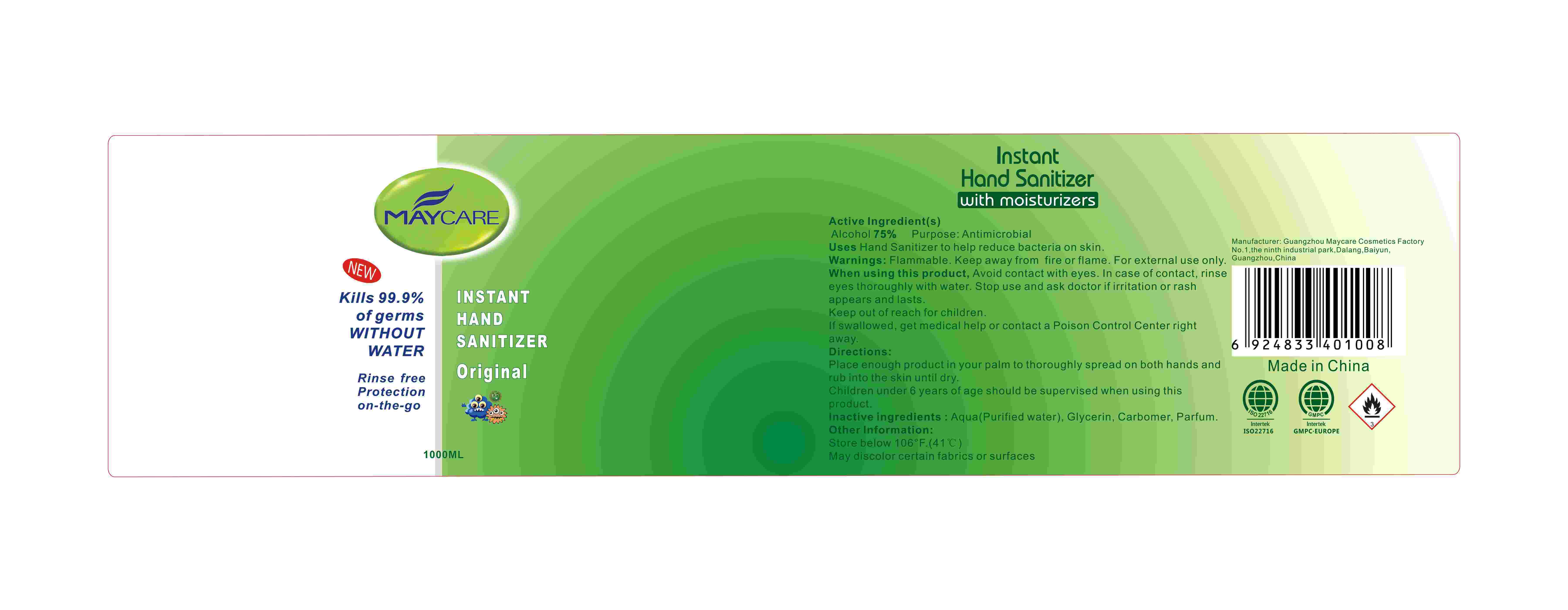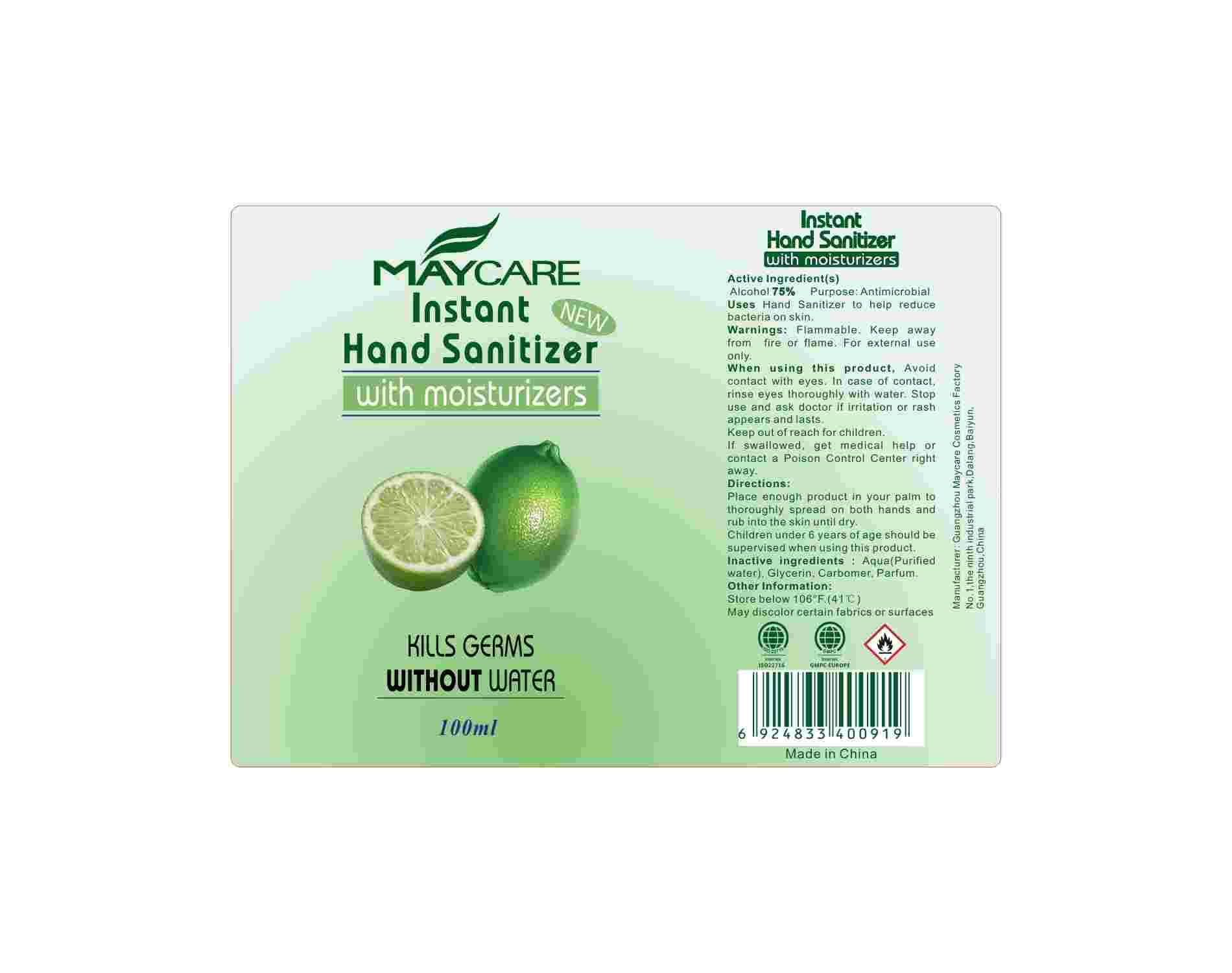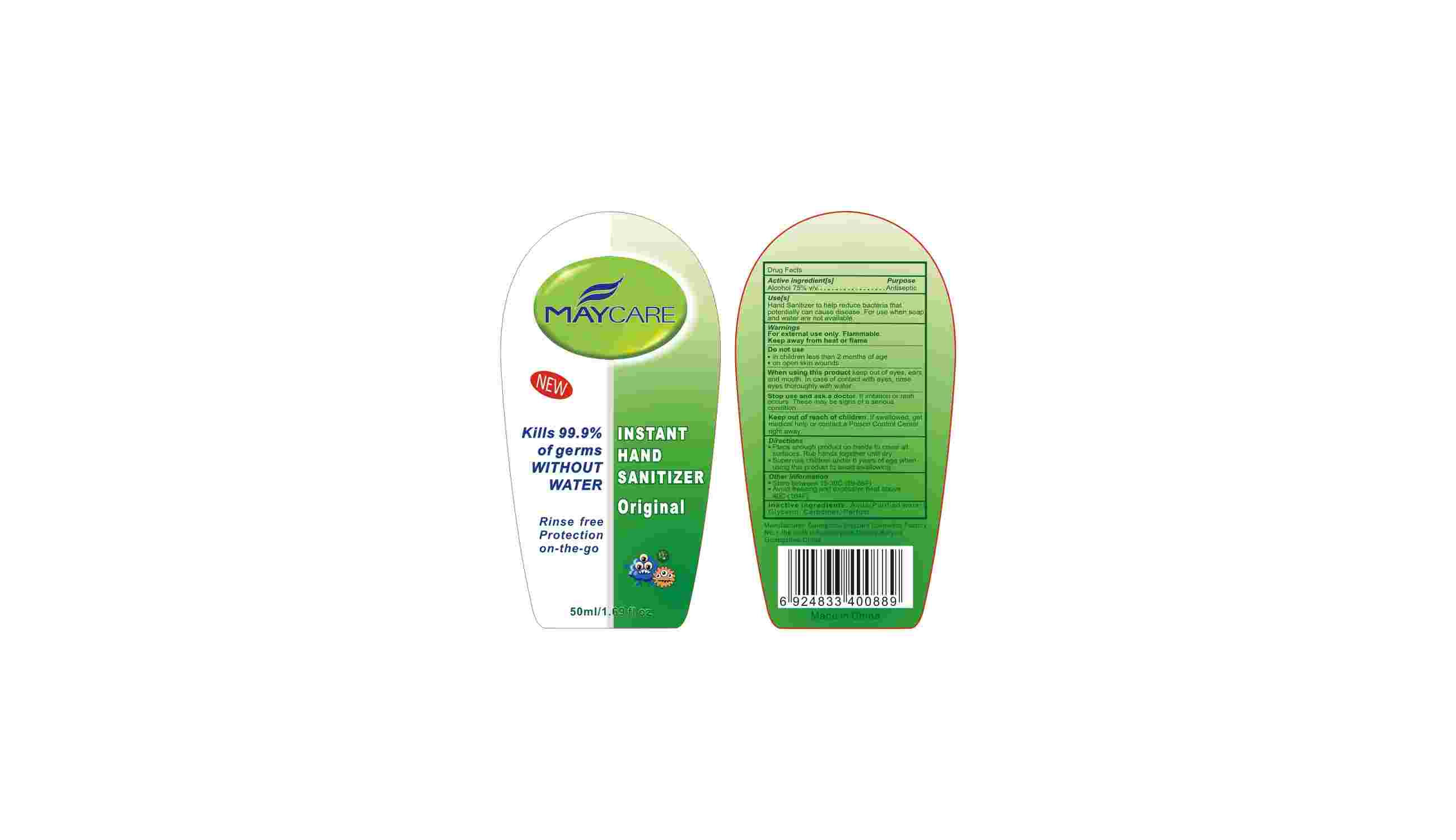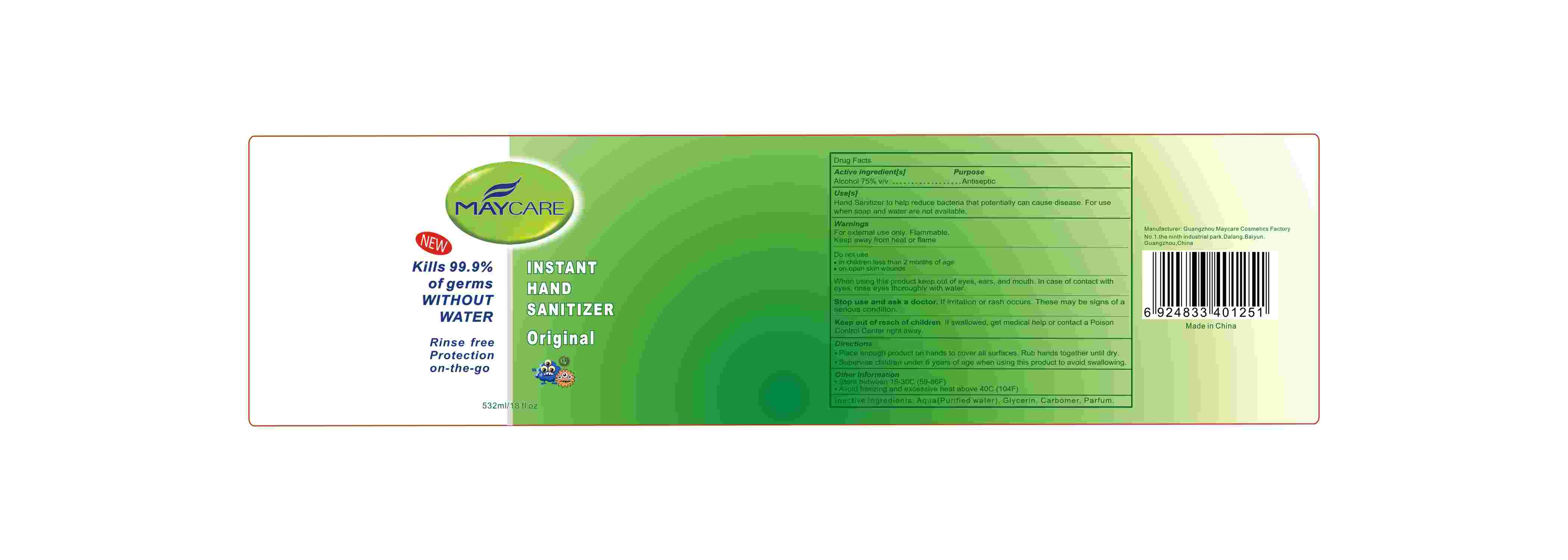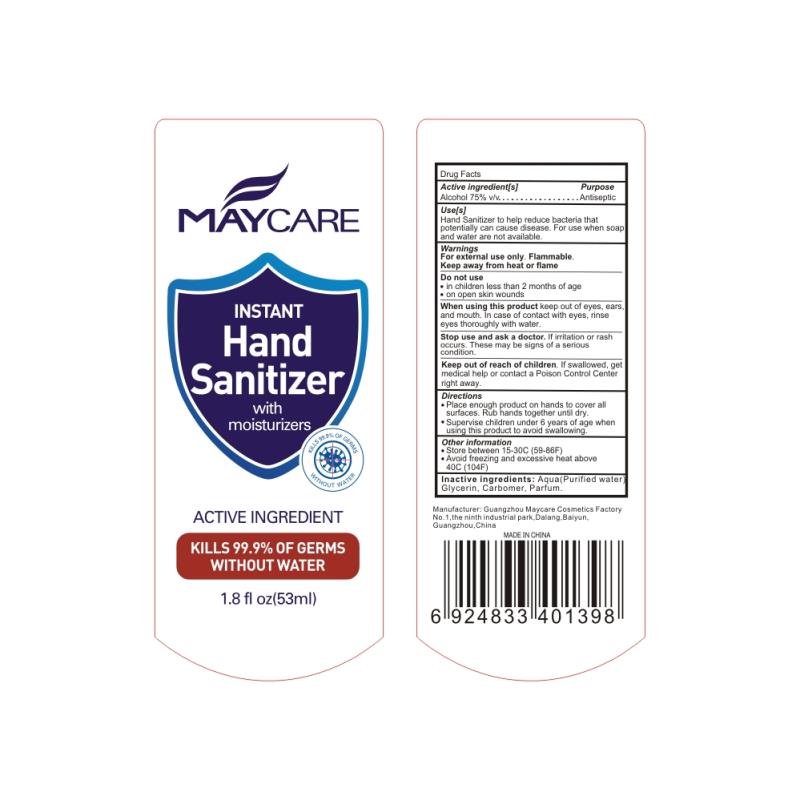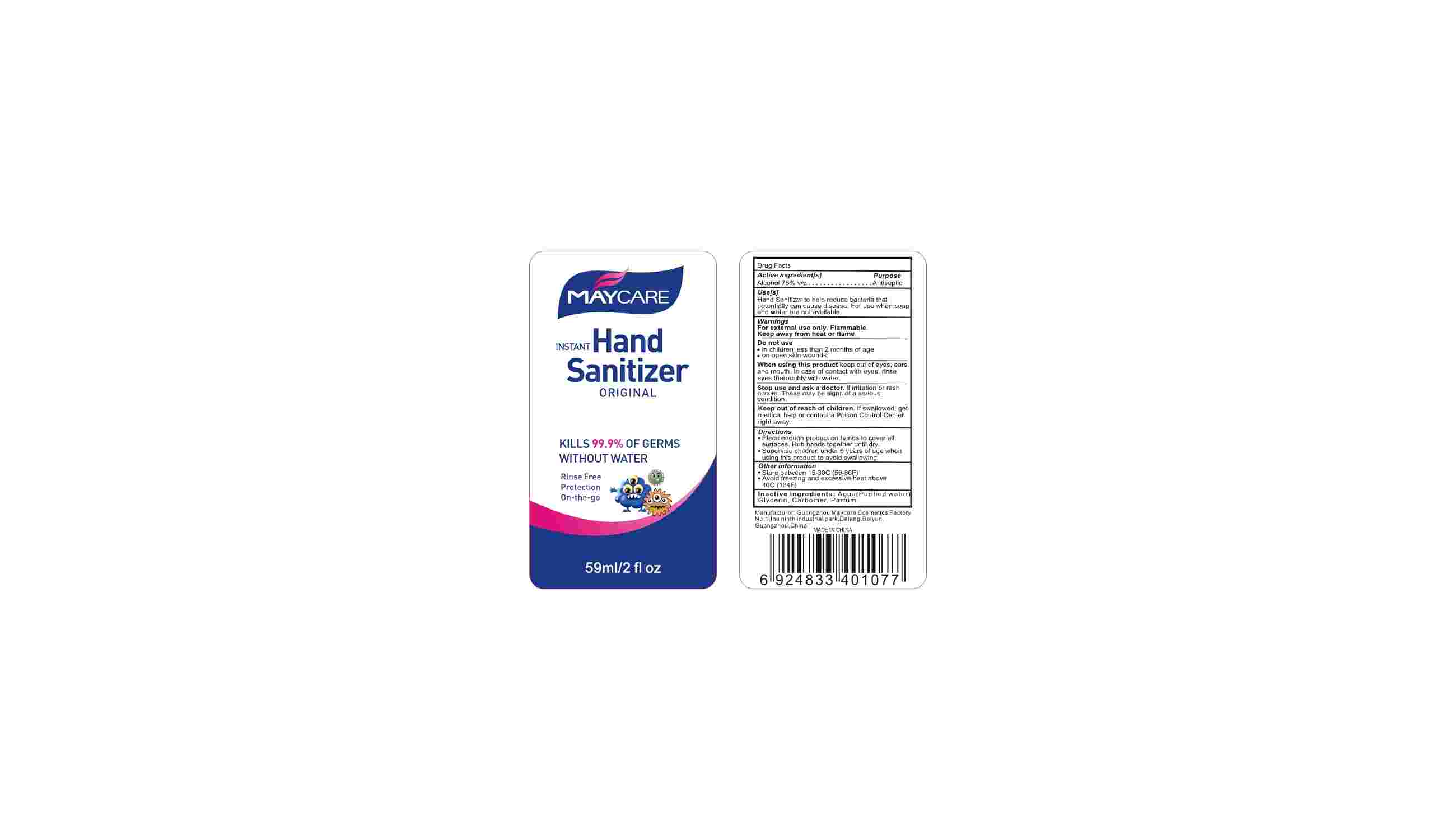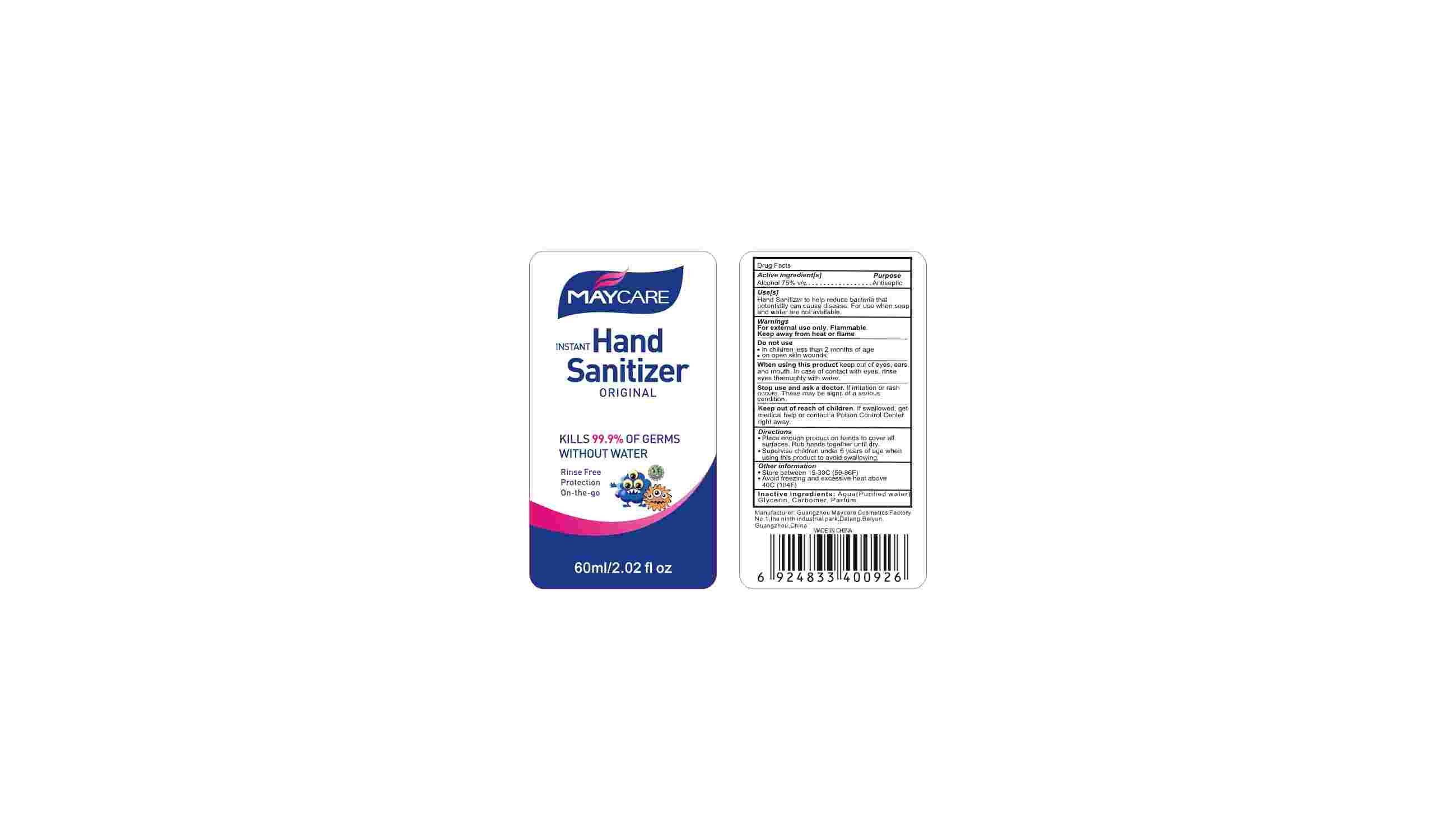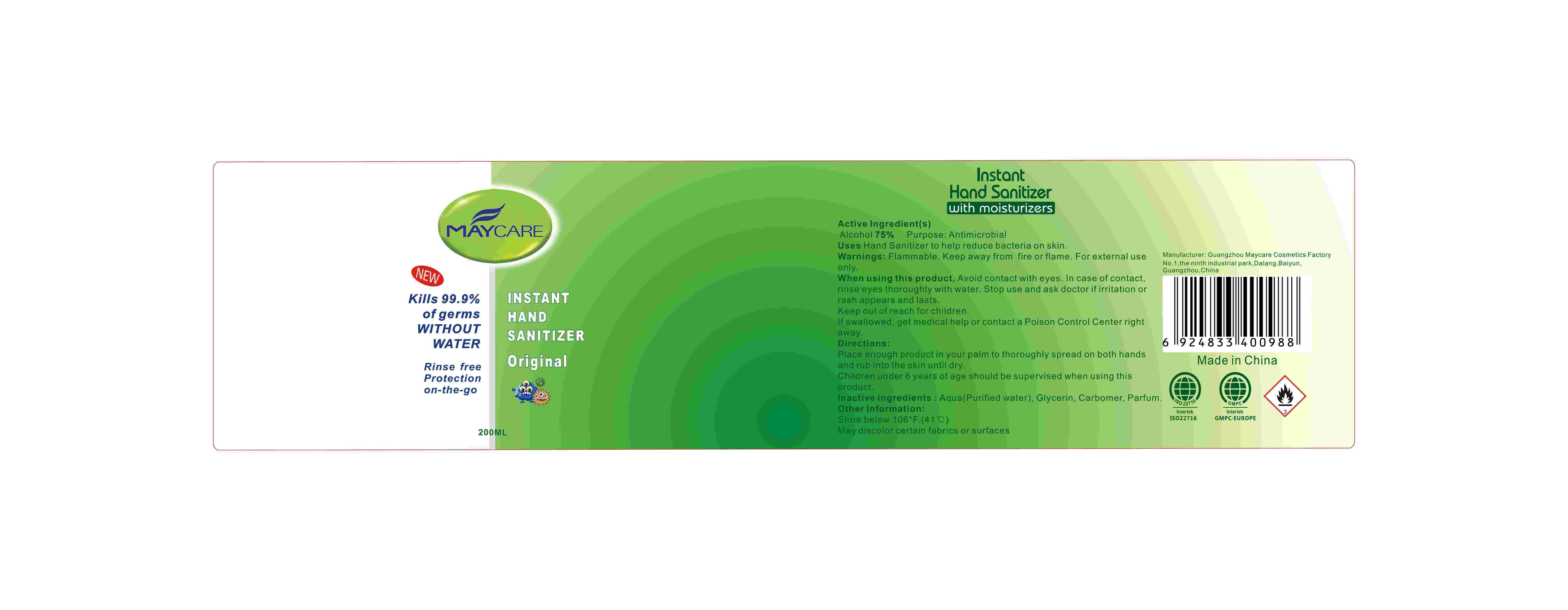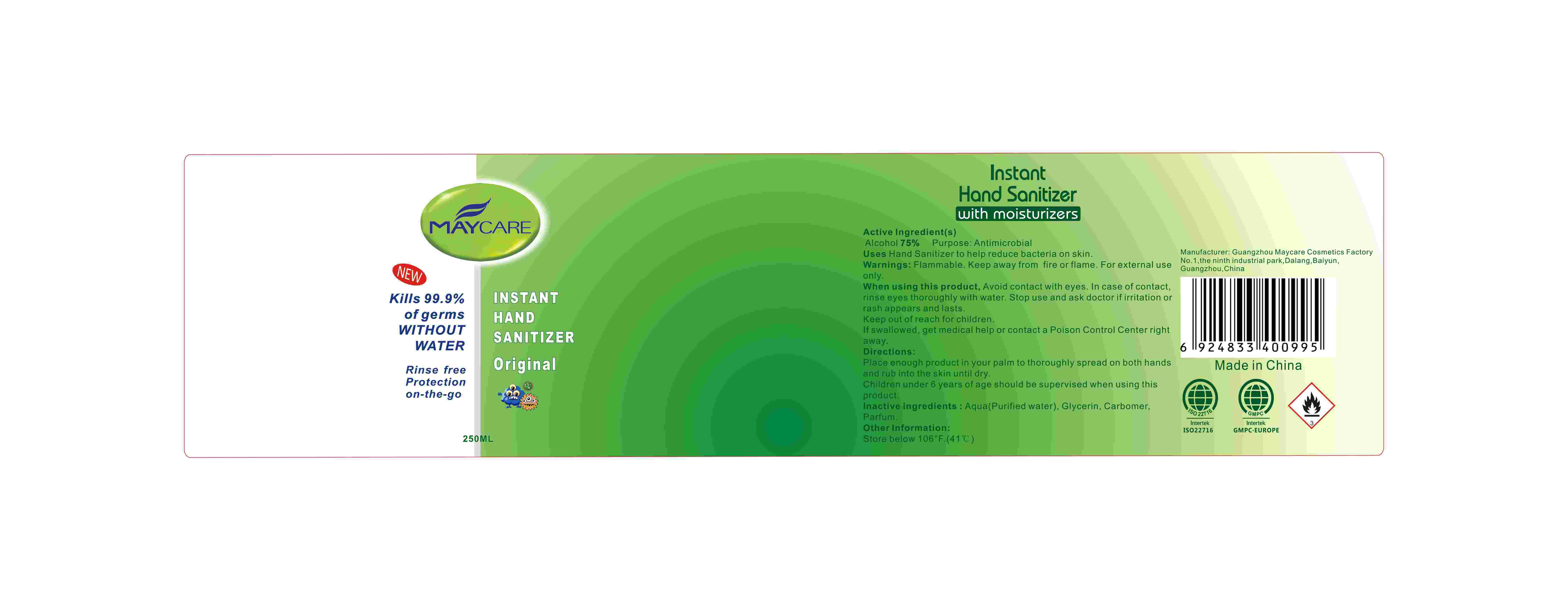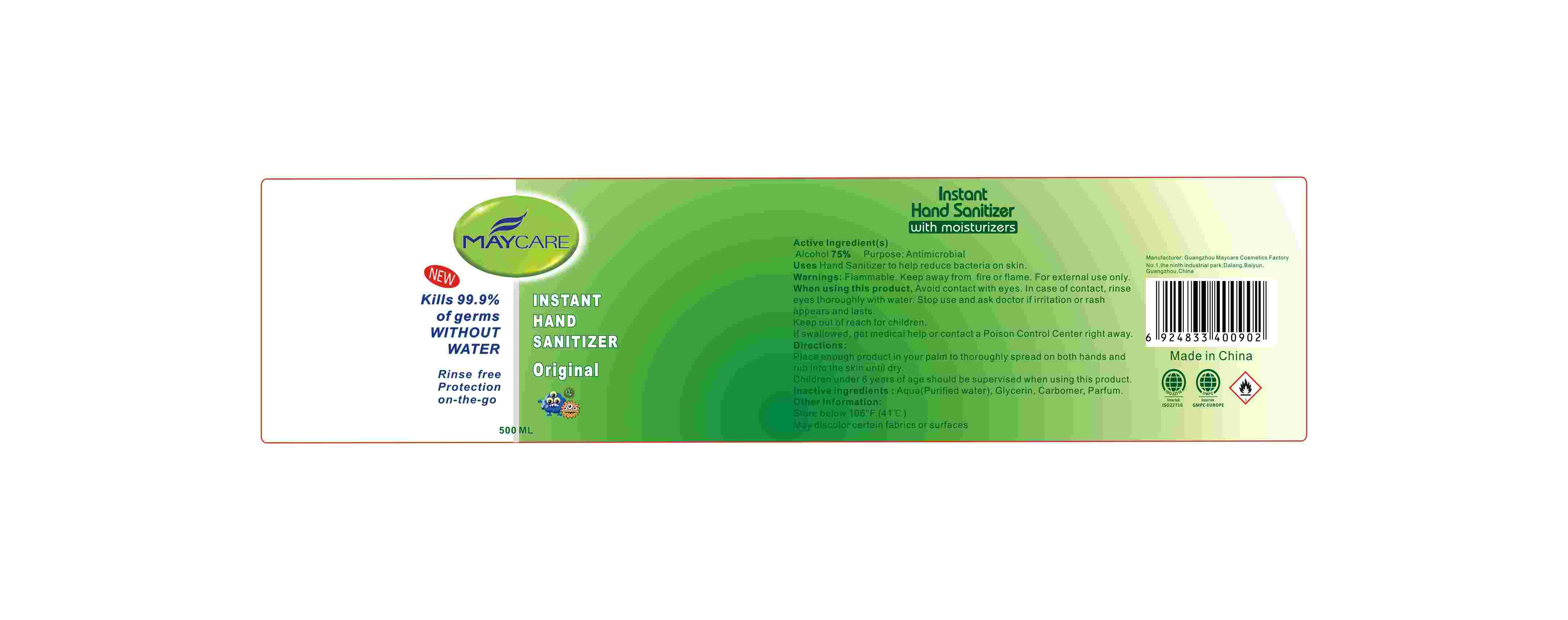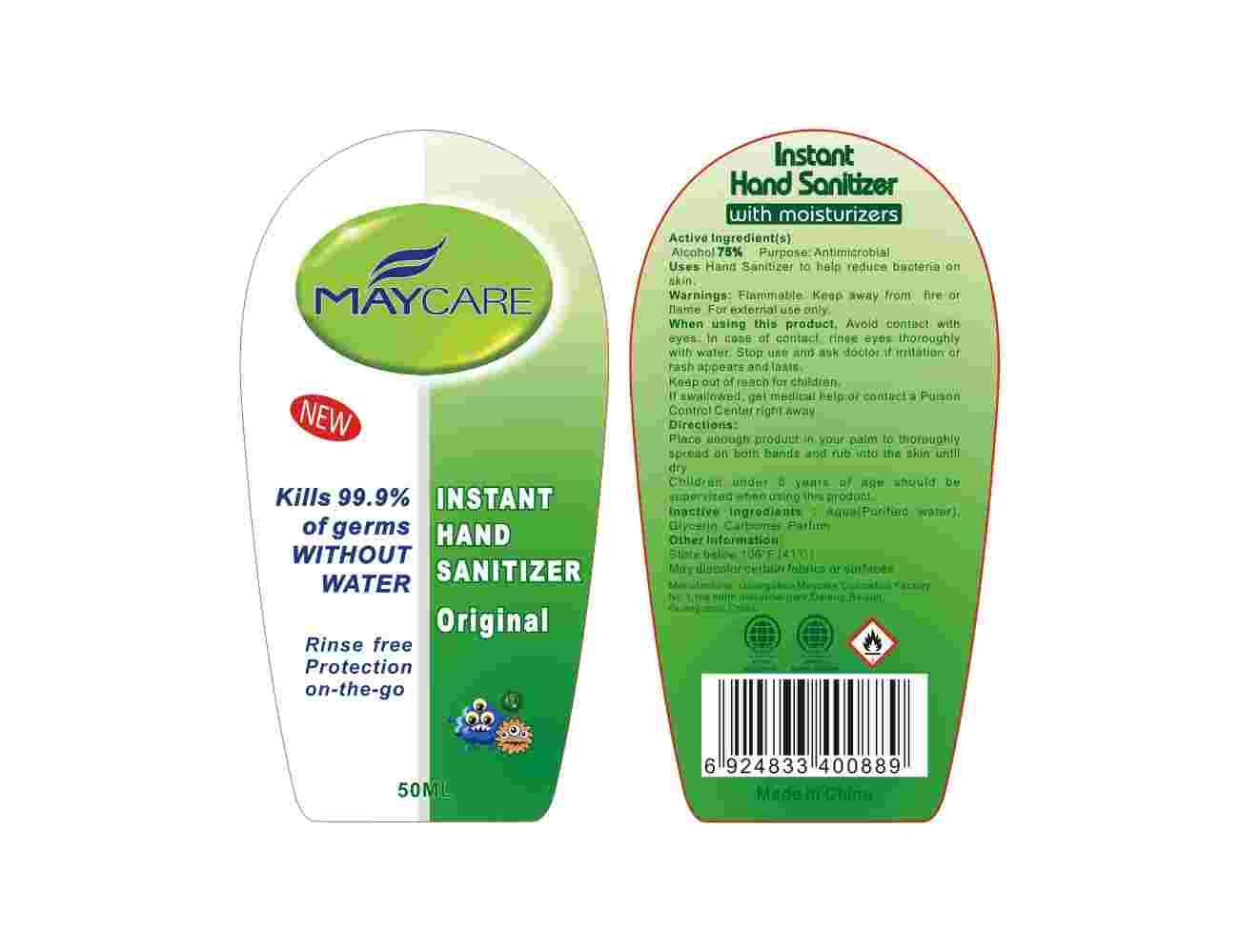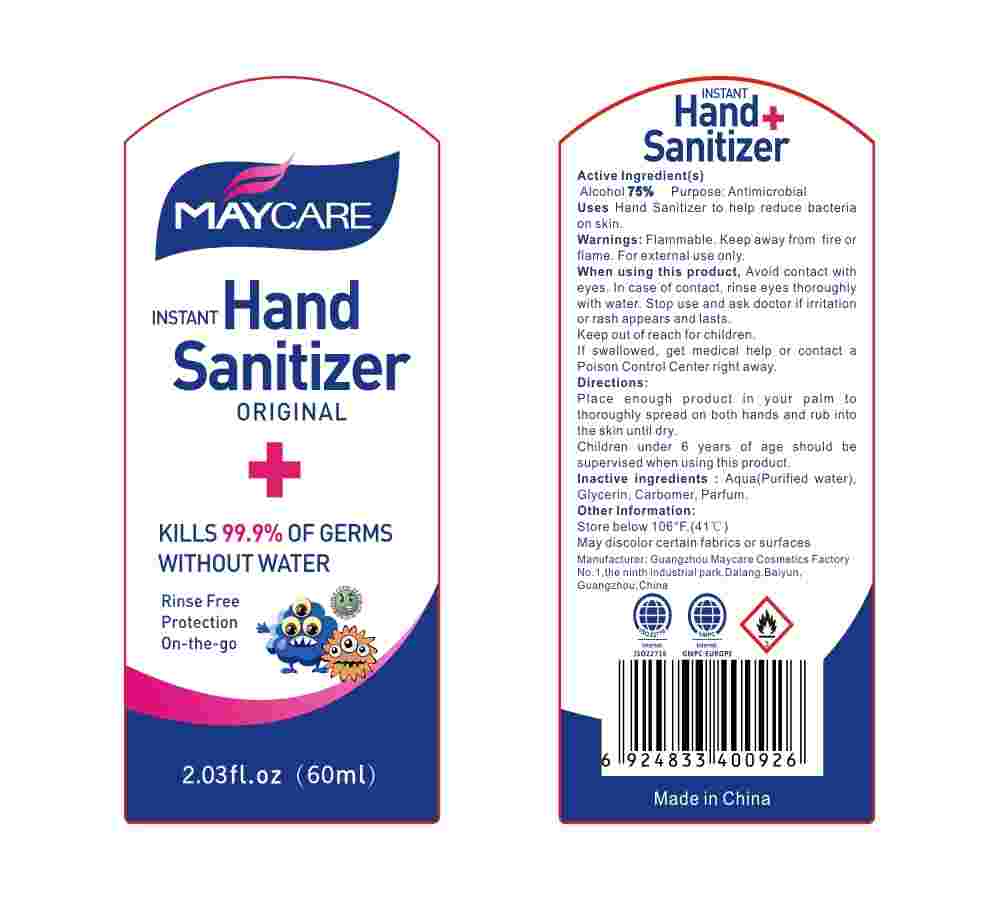 DRUG LABEL: INSTANT HAND SANITIZER Original
NDC: 75766-007 | Form: LIQUID
Manufacturer: Guangzhou Maycare Cosmetics Factory
Category: otc | Type: HUMAN OTC DRUG LABEL
Date: 20200522

ACTIVE INGREDIENTS: ALCOHOL 75 mL/100 mL
INACTIVE INGREDIENTS: METHYL BENZOATE 0.5 g/100 mL; GLYCERIN 2 g/100 mL; CARBOMER 934 1 g/100 mL; WATER

INSTANT HAND SANITIZER Original

Active Ingredient(s)

Alcohol 75% v/v. Purpose: Antiseptic

Purpose

Antimicrobial

Use

Hand Sanitizer to help reduce bacteria on skin

Warnings

Flammable. Keep away from fire or flame For external use only.

When using this product, Avoid contact with eyes. In case of contact, rinse eyes thoroughly with water Stop use and ask doctor if irritation or rash appears and lasts

Keep out of reach of children. If swallowed, get medical help or contact a Poison Control Center right away.

Directions

- Place enough product in your palm to thoroughly spread on both hands and rub into the skin until dry
- Children under 6 years of age should be supervised when using this product

Inactive ingredients

Aqua(Purified water),Glycerin,Carbomer,Parfum

Other information

Store below 106 F(41 C)May discolor certain fabrics or surfaces